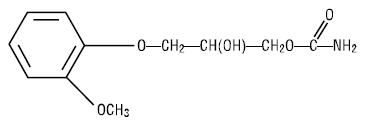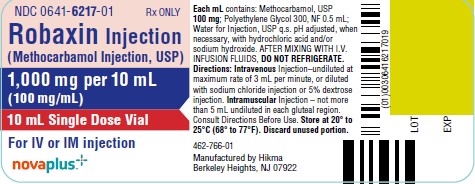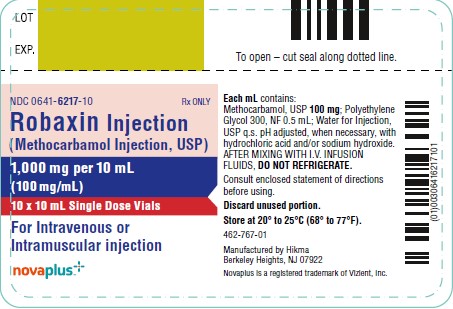 DRUG LABEL: ROBAXIN
NDC: 0641-6217 | Form: INJECTION
Manufacturer: Hikma Pharmaceuticals USA Inc.
Category: prescription | Type: HUMAN PRESCRIPTION DRUG LABEL
Date: 20240410

ACTIVE INGREDIENTS: METHOCARBAMOL 100 mg/1 mL
INACTIVE INGREDIENTS: POLYETHYLENE GLYCOL 300 0.5 mL/1 mL; WATER; HYDROCHLORIC ACID; SODIUM HYDROXIDE

ROBAXIN Injectable
(methocarbamol injection, USP)

NOVAPLUS®

DESCRIPTION

ROBAXIN (methocarbamol injection, USP) Injectable, a carbamate derivative of guaifenesin, is a central nervous system (CNS) depressant with sedative and musculoskeletal relaxant properties. It is a sterile, pyrogen-free solution intended for intramuscular or intravenous administration.

Each mL contains: methocarbamol, USP 100 mg, polyethylene glycol 300, NF 0.5 mL, Water for Injection, USP q.s. The pH is adjusted, when necessary, with hydrochloric acid and/or sodium hydroxide. The chemical name of methocarbamol is 3‑(2‑methoxyphenoxy)‑1,2-propanediol 1‑carbamate and has the empirical formula of C11H15NO5. Its molecular weight is 241.24. The structural formula is shown below:

Methocarbamol is a white powder, sparingly soluble in water and chloroform, soluble in alcohol (only with heating) and propylene glycol, and insoluble in benzene and n‑hexane.

ROBAXIN Injectable has a pH between 3.5 and 6.0.

AFTER MIXING WITH I.V. INFUSION FLUIDS, DO NOT REFRIGERATE.

CLINICAL PHARMACOLOGY

The mechanism of action of methocarbamol in humans has not been established, but may be due to general CNS depression. It has no direct action on the contractile mechanism of striated muscle, the motor end plate or the nerve fiber.

Pharmacokinetics

In healthy volunteers, the plasma clearance of methocarbamol ranges between 0.20 and 0.80 L/h/kg, the mean plasma elimination half-life ranges between 1 and 2 hours, and the plasma protein binding ranges between 46% and 50%.

Methocarbamol is metabolized via dealkylation and hydroxylation. Conjugation of methocarbamol also is likely. Essentially all methocarbamol metabolites are eliminated in the urine. Small amounts of unchanged methocarbamol also are excreted in the urine.

SPECIAL POPULATIONS

Elderly

The mean (± SD) elimination half-life of methocarbamol in elderly healthy volunteers (mean (± SD) age, 69 (± 4) years) was slightly prolonged compared to a younger (mean (± SD) age, 53.3 (± 8.8) years), healthy population (1.5 (± 0.4) hours versus 1.1 (± 0.27) hours, respectively). The fraction of bound methocarbamol was slightly decreased in the elderly versus younger volunteers (41 to 43% versus 46 to 50%, respectively).

Renally Impaired

The clearance of methocarbamol in 8 renally-impaired patients on maintenance hemodialysis was reduced about 40% compared to 17 normal subjects, although the mean (± SD) elimination half-life in these two groups was similar (1.2 (± 0.6) versus 1.1 (± 0.3) hours, respectively).

Hepatically Impaired

In 8 patients with cirrhosis secondary to alcohol abuse, the mean total clearance of methocarbamol was reduced approximately 70% compared to that obtained in 8 age- and weight-matched normal subjects. The mean (± SD) elimination half-life in the cirrhotic patients and the normal subjects was 3.38 (± 1.62) hours and 1.11 (± 0.27) hours respectively. The percent of methocarbamol bound to plasma proteins was decreased to approximately 40 to 45% compared to 46 to 50% in the normal subjects.

INDICATIONS AND USAGE

The injectable form of methocarbamol is indicated as an adjunct to rest, physical therapy, and other measures for the relief of discomfort associated with acute, painful musculoskeletal conditions. The mode of action of this drug has not been clearly identified, but may be related to its sedative properties. Methocarbamol does not directly relax tense skeletal muscles in man.

CONTRAINDICATIONS

ROBAXIN Injectable should not be administered to patients with known or suspected renal pathology. This caution is necessary because of the presence of polyethylene glycol 300 in the vehicle.

A much larger amount of polyethylene glycol 300 than is present in recommended doses of ROBAXIN Injectable is known to have increased pre-existing acidosis and urea retention in patients with renal impairment. Although the amount present in this preparation is well within the limits of safety, caution dictates this contraindication.

ROBAXIN Injectable is contraindicated in patients hypersensitive to methocarbamol or to any of the injection components.

WARNINGS

Since methocarbamol may possess a general CNS depressant effect, patients receiving ROBAXIN Injectable should be cautioned about combined effects with alcohol and other CNS depressants.

Safe use of ROBAXIN Injectable has not been established with regard to possible adverse effects upon fetal development. There have been very rare reports of fetal and congenital abnormalities following in utero exposure to methocarbamol. Therefore, ROBAXIN Injectable should not be used in women who are or may become pregnant and particularly during early pregnancy unless in the judgment of the physician the potential benefits outweigh the possible hazards (see PRECAUTIONS, Pregnancy).

Use in Activities Requiring Mental Alertness

Methocarbamol may impair mental and/or physical abilities required for performance of hazardous tasks, such as operating machinery or driving a motor vehicle. Patients should be cautioned about operating machinery, including automobiles, until they are reasonably certain that methocarbamol therapy does not adversely affect their ability to engage in such activities.

PRECAUTIONS

General

As with other agents administered either intravenously or intramuscularly, careful supervision of dose and rate of injection should be observed. Rate of injection should not exceed 3 mL per minute–i.e., one 10 mL vial in approximately three minutes. Since ROBAXIN Injectable is hypertonic, vascular extravasation must be avoided. A recumbent position will reduce the likelihood of side reactions.

Blood aspirated into the syringe does not mix with the hypertonic solution. This phenomenon occurs with many other intravenous preparations. The blood may be injected with the methocarbamol, or the injection may be stopped when the plunger reaches the blood, whichever the physician prefers.

The total dosage should not exceed 30 mL (three vials) a day for more than three consecutive days except in the treatment of tetanus.

Caution should be observed in using the injectable form in patients with suspected or known seizure disorders.

Information for Patients

Patients should be cautioned that methocarbamol may cause drowsiness or dizziness, which may impair their ability to operate motor vehicles or machinery.

Because methocarbamol may possess a general CNS-depressant effect, patients should be cautioned about combined effects with alcohol and other CNS depressants.

Drug Interactions

See WARNINGS and PRECAUTIONS for interaction with CNS drugs and alcohol.

Methocarbamol may inhibit the effect of pyridostigmine bromide. Therefore, methocarbamol should be used with caution in patients with myasthenia gravis receiving anticholinesterase agents.

Drug/Laboratory Test Interactions

Methocarbamol may cause a color interference in certain screening tests for 5‑hydroxyindoleacetic acid (5-HIAA) using nitrosonaphthol reagent and in screening tests for urinary vanillylmandelic acid (VMA) using the Gitlow method.

Carcinogenesis, Mutagenesis, Impairment of Fertility

Long-term studies to evaluate the carcinogenic potential of methocarbamol have not been performed. No studies have been conducted to assess the effect of methocarbamol on mutagenesis or its potential to impair fertility.

Pregnancy

Teratogenic Effects-Pregnancy Category C

Animal reproduction studies have not been conducted with methocarbamol. It is also not known whether methocarbamol can cause fetal harm when administered to a pregnant woman or can affect reproduction capacity. ROBAXIN Injectable should be given to a pregnant woman only if clearly needed.

Safe use of ROBAXIN Injectable has not been established with regard to possible adverse effects upon fetal development. There have been reports of fetal and congenital abnormalities following in utero exposure to methocarbamol. Therefore, ROBAXIN Injectable should not be used in women who are or may become pregnant and particularly during early pregnancy unless in the judgment of the physician the potential benefits outweigh the possible hazards (see WARNINGS).

Nursing Mothers

Methocarbamol and/or its metabolites are excreted in the milk of dogs; however, it is not known whether methocarbamol or its metabolites are excreted in human milk. Because many drugs are excreted in human milk, caution should be exercised when ROBAXIN Injectable is administered to a nursing woman.

Pediatric Use

Safety and effectiveness of ROBAXIN Injectable in pediatric patients have not been established except in tetanus. See DOSAGE AND ADMINISTRATION, Special Directions for Use in Tetanus, For Pediatric Patients.

ADVERSE REACTIONS

The following adverse reactions have been reported coincident with the administration of methocarbamol. Some events may have been due to an overly rapid rate of intravenous injection.

Body as a whole: Anaphylactic reaction, angioneurotic edema, fever, headache

Cardiovascular system: Bradycardia, flushing, hypotension, syncope, thrombophlebitis

In most cases of syncope there was spontaneous recovery. In others, epinephrine, injectable steroids, and/or injectable antihistamines were employed to hasten recovery.

Digestive system: Dyspepsia, jaundice (including cholestatic jaundice), nausea and vomiting

Hemic and lymphatic system: Leukopenia

Immune system: Hypersensitivity reactions

Nervous system: Amnesia, confusion, diplopia, dizziness or light-headedness, drowsiness, insomnia, mild muscular incoordination, nystagmus, sedation, seizures (including grand mal), vertigo

The onset of convulsive seizures during intravenous administration of methocarbamol has been reported in patients with seizure disorders. The psychic trauma of the procedure may have been a contributing factor. Although several observers have reported success in terminating epileptiform seizures with ROBAXIN Injectable, its administration to patients with epilepsy is not recommended (see PRECAUTIONS, General).

Skin and special senses: Blurred vision, conjunctivitis, nasal congestion, metallic taste, pruritus, rash, urticaria

Other: Pain and sloughing at the site of injection

OVERDOSAGE

Limited information is available on the acute toxicity of methocarbamol. Overdose of methocarbamol is frequently in conjunction with alcohol or other CNS depressants and includes the following symptoms: nausea, drowsiness, blurred vision, hypotension, seizures, and coma. In post-marketing experience deaths have been reported with an overdose of methocarbamol alone or in the presence of other CNS depressants, alcohol or psychotropic drugs.

Treatment

Management of overdose includes symptomatic and supportive treatment. Supportive measures include maintenance of an adequate airway, monitoring urinary output and vital signs, and administration of intravenous fluids if necessary. The usefulness of hemodialysis in managing overdose is unknown.

DOSAGE AND ADMINISTRATION

For Intravenous and Intramuscular Use Only. Total adult dosage should not exceed 30 mL (3 vials) a day for more than 3 consecutive days except in the treatment of tetanus. If the condition persists, a like course may be repeated after a drug-free interval of 48 hours. Dosage and frequency of injection should be based on the severity of the condition being treated and therapeutic response noted.

For the relief of symptoms of moderate degree, one dose of 1 gram (one 10 mL vial) may be adequate. Ordinarily this injection need not be repeated, as the administration of the oral form will usually sustain the relief initiated by the injection. For the severest cases or in postoperative conditions in which oral administration is not feasible, additional doses of 1 gram may be repeated every 8 hours up to a maximum of 3 g/day for no more than 3 consecutive days.

Directions for Intravenous Use

ROBAXIN Injectable may be administered undiluted directly into the vein at a maximum rate of three mL per minute. It may also be added to an intravenous drip of Sodium Chloride Injection (Sterile Isotonic Sodium Chloride Solution for Parenteral Use) or five percent Dextrose Injection (Sterile 5 percent Dextrose Solution); one vial given as a single dose should not be diluted to more than 250 mL for I.V. infusion. AFTER MIXING WITH I.V. INFUSION FLUIDS, DO NOT REFRIGERATE. Care should be exercised to avoid vascular extravasation of this hypertonic solution, which may result in thrombophlebitis. It is preferable that the patient be in a recumbent position during and for at least 10 to 15 minutes following the injection.

Directions for Intramuscular Use

When the intramuscular route is indicated, not more than five mL (one-half vial) should be injected into each gluteal region. The injections may be repeated at eight hour intervals, if necessary. When satisfactory relief of symptoms is achieved, it can usually be maintained with tablets.

Not Recommended for Subcutaneous Administration.

Special Directions for Use in Tetanus

There is clinical evidence which suggests that methocarbamol may have a beneficial effect in the control of the neuromuscular manifestations of tetanus. It does not, however, replace the usual procedure of debridement, tetanus antitoxin, penicillin, tracheotomy, attention to fluid balance, and supportive care. ROBAXIN Injectable should be added to the regimen as soon as possible.

For adults: Inject one or two vials directly into the tubing of the previously inserted indwelling needle. An additional 10 mL or 20 mL may be added to the infusion bottle so that a total of up to 30 mL (three vials) is given as the initial dose (see PRECAUTIONS). This procedure should be repeated every six hours until conditions allow for the insertion of a nasogastric tube. Crushed methocarbamol tablets suspended in water or saline may then be given through this tube. Total daily oral doses up to 24 grams may be required as judged by patient response.

For pediatric patients: A minimum initial dose of 15 mg/kg or 500 mg/m^2 is recommended. This dosage may be repeated every six hours, if required. The total dose should not exceed 1.8 g/m^2 for 3 consecutive days. The maintenance dosage may be given by injection into tubing or by I.V. infusion with an appropriate quantity of fluid. See directions for I.V. use.

HOW SUPPLIED

ROBAXIN Injectable (100 mg/mL) supplied in – 10 mL single dose vials in packages of 25 (NDC 0641-6217-25).

Store at 20°- 25°C (68°- 77°F), excursions permitted to 15°- 30°C (59°- 86°F).

Not made with natural rubber latex.

To report SUSPECTED ADVERSE REACTIONS, contact West-Ward Pharmaceuticals Corp. at 1-877-845-0689 or the FDA at 1-800-FDA-1088 or www.fda.gov/medwatch.

For Product Inquiry call 1-877-845-0689.

Manufactured by:

Hikma Pharmaceuticals USA Inc.
Berkeley Heights, NJ 07922

NOVAPLUS is a registered trademark of Vizient, Inc.
NOVAPLUS®

Revised February 2023

462-768-01

PRINCIPAL DISPLAY PANEL

NDC 0641-6217-01 Rx ONLY
ROBAXIN Injectable
(Methocarbamol Injection, USP)
1,000 mg/10 mL
(100 mg/mL)
10 mL Single Dose Vial

NDC 0641-6217-10 Rx ONLY
ROBAXIN Injectable
(Methocarbamol Injection, USP)
1,000 mg/10 mL
(100 mg/mL)
10 x 10 mL Single Dose Vials
FOR INTRAVENOUS OR
INTRAMUSCULAR INJECTION